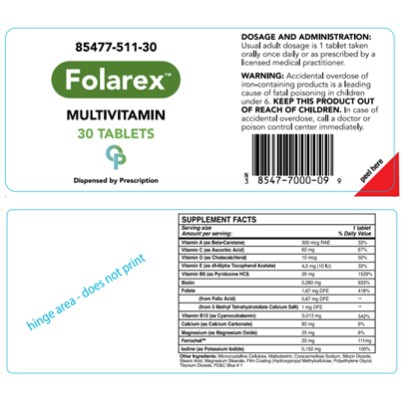 DRUG LABEL: Folartex
NDC: 85477-511 | Form: TABLET
Manufacturer: Oncora Pharma, LLC
Category: prescription | Type: HUMAN PRESCRIPTION DRUG LABEL
Date: 20260225

ACTIVE INGREDIENTS: BETA CAROTENE 300 ug/1 1; ASCORBIC ACID 60 mg/1 1; CHOLECALCIFEROL 10 ug/1 1; .ALPHA.-TOCOPHEROL ACETATE, DL- 4.5 mg/1 1; PYRIDOXINE HYDROCHLORIDE 26 mg/1 1; BIOTIN 0.28 mg/1 1; FOLIC ACID 1.67 mg/1 1; CYANOCOBALAMIN 0.013 mg/1 1; CALCIUM CARBONATE 80 mg/1 1; MAGNESIUM OXIDE 25 mg/1 1; FERROUS BISGLYCINATE 20 mg/1 1; POTASSIUM IODIDE 0.15 mg/1 1
INACTIVE INGREDIENTS: CELLULOSE, MICROCRYSTALLINE; MALTODEXTRIN; CROSCARMELLOSE SODIUM; SILICON DIOXIDE; STEARIC ACID; MAGNESIUM STEARATE; HYDROXYPROPYL METHYLCELLULOSE; POLYETHYLENE GLYCOL 1000; TITANIUM DIOXIDE; FD&C BLUE NO. 1

Folarex

Folarex

DESCRIPTION

Folarex is a prescription multivitamin/multimineral dietary supplement.

SUPPLEMENT FACTS
Servingsize Amount per serving: |  | 1tablet % Daily Value
Vitamin A (as Beta-Carotene) | 300 mcg RAE | 33%
Vitamin C (as Ascorbic Acid) | 60mg | 67%
Vitamin D (as Cholecalciferol) | 10mcg | 50%
Vitamin E (as di-Alpha Tocopherol Acetate) | 4.5 mg (10 IU) | 33%
Vitamin 86 (as Pyrldoxine HCI) | 26mg | 1529%
Biotin | 0.280mg | 933%
Folate | 1.67 mg DFE | 418%
(from Folic Acid) | 0.67 mg DFE
(from 5 Methyl Tetrahydrotolate Calcium Salt) | 1 mg DFE
Vitamin 812 (as Cyanocobalamin) | 0.013 mg | 542%
Calcium (as Calcium Carbonate) | 80 mg | 6%
Magnesium (as Magnesium Oxide) | 25mg | 6%
Ferrochel"" | 20mg | 111mg
Iodine (as Potassium Iodide) | 0.150mg | 100%

Other Ingredients: Microcrysta line Ce lulose, Maltodextrin, Croscarme lose Sodium, Silcon Dioxide, Stearic Acid, Magnesium Stearate, FiIm Coating (Hydroxypropyl Methylce lulose, Polyethylene Glycol, Titanium Dioxide, FD&C Blue# 1

INDICATIONS AND USAGE

Folarex is a prescription multivitamin/multi-mineral dietary supplement formulated for the clinical dietary management of a suboptimal nutritional status in patients where advanced folate, vitamin B supplementation, and maintenance of good health is needed.

CONTRAINDICATIONS

Folarex is contraindicated in patients with a known hypersensitivity to any of the ingredients.

PRECAUTIONS

Folic acid alone is improper therapy in the treatment of pernicious anemia and other megaloblastic anemias where Vitamin B 12 deficient. Folic acid in doses above 1.0 mg daily may obscure pernicious anemia in that hematologic remission can occur while neurological manifestations progress.

WARNINGS

WARNING Accidental overdose of iron-containing products is a leading cause of fatal poising in children under 6. KEEP THIS PRODUCT OUT OF REACH OF CHILDREN. In the case of accidental overdose, ca l a doctor or poison control center immediately.

ADVERSE REACTIONS

Allergic sensitization has been reported fo lowing both oral and parenteral administration of folic acid. You should ca l your doctor for medical advice about serious adverse events. To reports adverse side effects or to obtain product information, contact Oncora Pharma at 888-321-2821.

DOSAGE AND ADMINISTRATION

One tablet daily or as directed by a physician.

HOW SUPPLIED

Bottles of 30 Tablets (85477-901-30). Tablet is tan, oblong.

STORAGE

STORAGE: Store at 20- 25 degree C (68-77 F) excersions permitted to 15-30 degree C (59-86 F) {See USP contro led Room Temperature} Avoid excessive heat, light and moisture.

TAMPER EVIDENT: Do not use if seal is broken or missing. MADE IN USA
Distributed by:
888-321-2821
Oncora Pharma Da las, TX 75161

PRINCIPAL DISPLAY PANEL

85477-511-30
Folarex
MULTIVITAMIN
30 TABLETS

Oncora Pharma, LLC